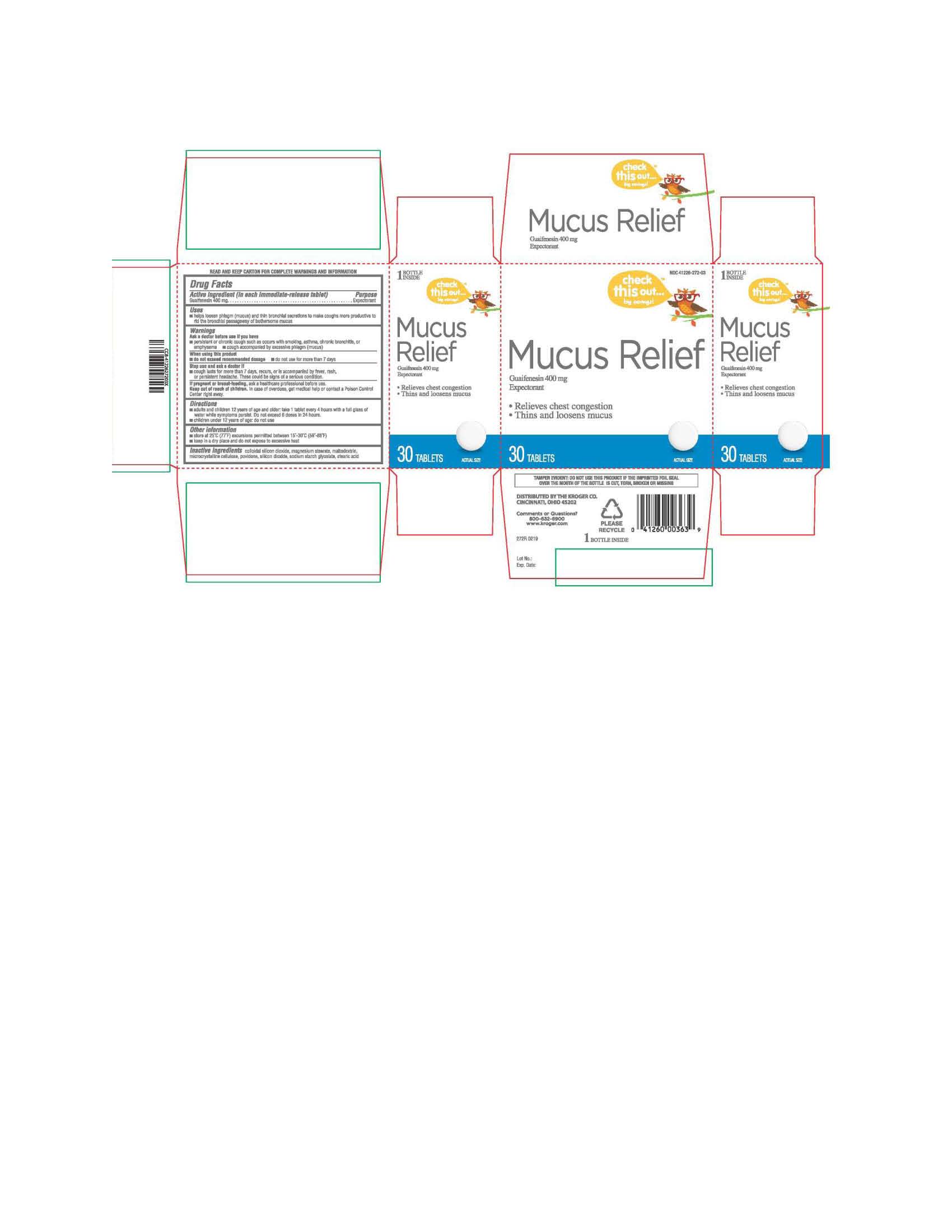 DRUG LABEL: MUCUS RELIEF
NDC: 41226-272 | Form: TABLET
Manufacturer: KROGER COMPANY
Category: otc | Type: HUMAN OTC DRUG LABEL
Date: 20190515

ACTIVE INGREDIENTS: GUAIFENESIN 400 mg/1 1
INACTIVE INGREDIENTS: SODIUM STARCH GLYCOLATE TYPE A POTATO; MAGNESIUM STEARATE; MALTODEXTRIN; MICROCRYSTALLINE CELLULOSE; POVIDONE; STEARIC ACID; SILICON DIOXIDE

272R - KROGER MUCUS RELIEF

ACTIVE INGREDIENT

Each immediate release tablet contains: Guaifenesin 400 mg

INACTIVE INGREDIENT

Silicon Dioxide, Magnesium Stearate, Maltodextrin, Cellulose, Microcrystalline, Povidone, Sodium Starch Glycolate, Stearic Acid

PURPOSE: EXPECTORANT

INDICATIONS AND USAGE

Helps loosen phlegm (mucus) and thin

bronchial secretions to make coughs more productive to rid the bronchial passageway of bothersome mucus.

DOSAGE AND ADMINISTRATION

Adults and children 12 years of age and older, take 1 tablet every 4 hours with a full glass of water while symptoms persist. Do not exceed 6 doses in 24 hours. Children under 12 years of age do not us

Ask a doctor before use if you have: Persistent or chronic cough such as occurs with smoking, asthma, chronic bronchitis, or emphysema; Cough accompanied by excessive phlegm (mucus)

Keep Out of Reach of Children: In case of overdose, get medical help or contact a Poison Control Center